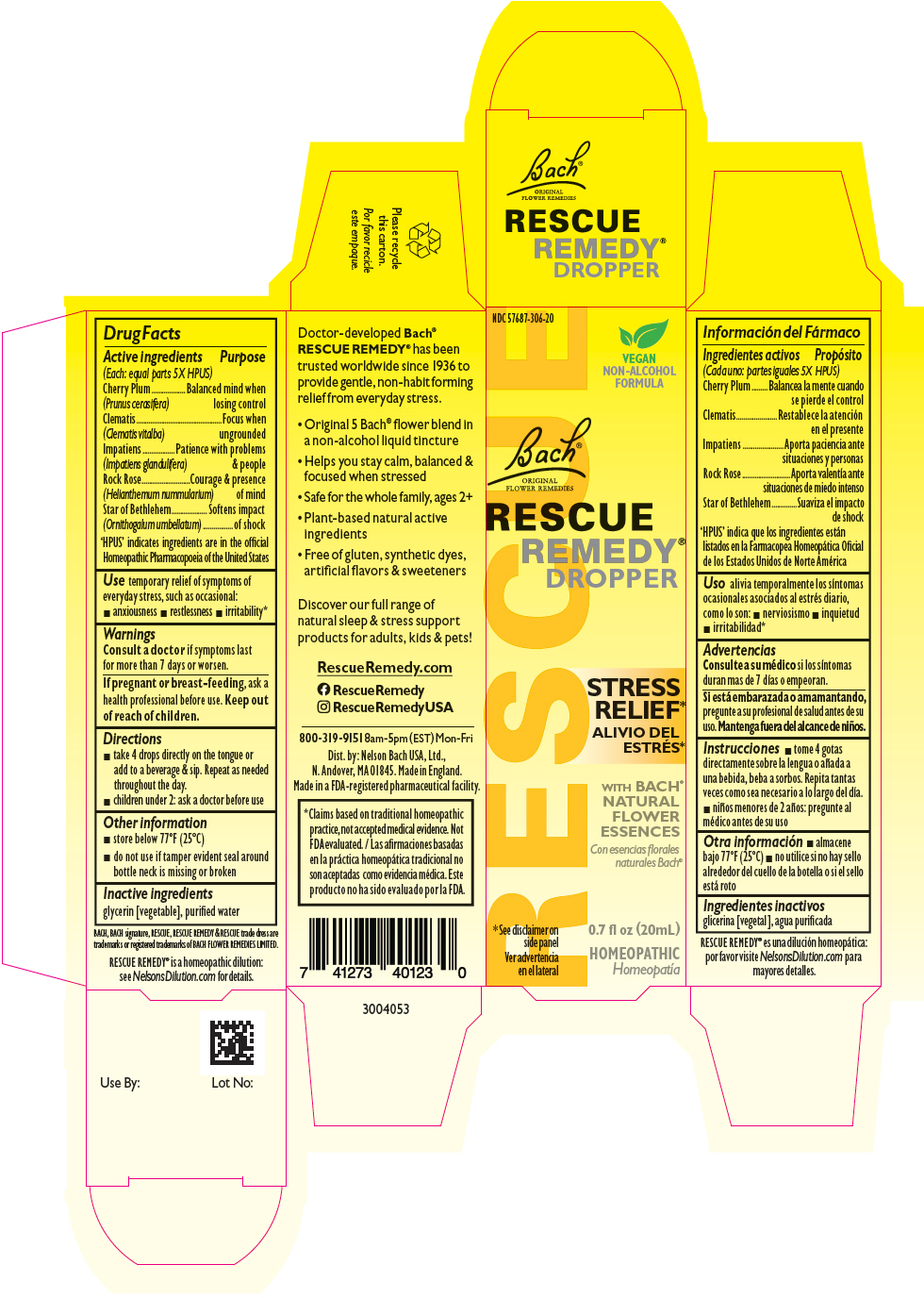 DRUG LABEL: Rescue Remedy 
NDC: 57687-306 | Form: SOLUTION
Manufacturer: Nelson Bach USA Limited
Category: homeopathic | Type: HUMAN OTC DRUG LABEL
Date: 20220106

ACTIVE INGREDIENTS: Helianthemum nummularium flower 5 [hp_X]/0.095 mL; Clematis vitalba flower 5 [hp_X]/0.095 mL; Impatiens glandulifera flower 5 [hp_X]/0.095 mL; Prunus cerasifera flower 5 [hp_X]/0.095 mL; ORNITHOGALUM UMBELLATUM WHOLE 5 [hp_X]/0.095 mL
INACTIVE INGREDIENTS: glycerin; WATER

Rescue Remedy®
Dropper

Drug Facts

ACTIVE INGREDIENT

Active ingredients (Each: equal parts 5X HPUS) | Purpose
Cherry Plum (Prunus cerasifera) | Balanced mind when losing control
Clematis (Clematis vitalba) | Focus when ungrounded
Impatiens (Impatiens glandulifera) | Patience with problems & people
Rock Rose (Helianthemum nummularium) | Courage & presence of mind
Star of Bethlehem (Ornithogalum umbellatum) | Softens impact of shock

'HPUS' indicates ingredients are in the official Homeopathic Pharmacopoeia of the United States

Use

temporary relief of symptoms of everyday stress, such as occasional:

- anxiousness
- restlessness
- irritability [Claims based on traditional homeopathic practice, not accepted medical evidence. Not FDA evaluated.]

Warnings

ASK DOCTOR

Consult a doctor if symptoms last for more than 7 days or worsen.

PREGNANCY OR BREAST FEEDING

If pregnant or breast-feeding, ask a health professional before use.

Keep out of reach of children.

Directions

- take 4 drops directly on the tongue or add to a beverage & sip. Repeat as needed throughout the day.
- children under 2: ask a doctor before use

Other information

- store below 77°F (25°C)
- do not use if tamper evident seal around bottle neck is missing or broken

Inactive ingredients

glycerin [vegetable], purified water

Dist. by: Nelson Bach USA, Ltd.,
N. Andover, MA 01845.

PRINCIPAL DISPLAY PANEL - 20 mL Bottle Carton

NDC 57687-306-20

VEGAN
NON-ALCOHOL
FORMULA

Bach®
ORIGINAL
FLOWER REMEDIES

RESCUE
REMEDY®
DROPPER

STRESS
RELIEF*

WITH BACH®
NATURAL
FLOWER
ESSENCES

0.7 fl oz (20mL)

HOMEOPATHIC

* See disclaimer on
side panel